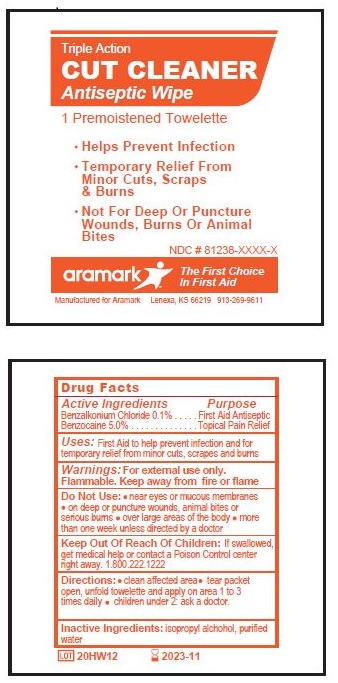 DRUG LABEL: CUT CLEANER
NDC: 81238-4616 | Form: CLOTH
Manufacturer: Western First Aid Safety dba Aramark
Category: otc | Type: HUMAN OTC DRUG LABEL
Date: 20210521

ACTIVE INGREDIENTS: BENZALKONIUM CHLORIDE 0.45 mg/0.45 g; BENZOCAINE 22.5 mg/0.45 g
INACTIVE INGREDIENTS: ISOPROPYL ALCOHOL; WATER

aramark CUT CLEANER Antiseptic Wipe

Drug Facts

Active Ingredients

Benzalkonium Chloride 0.1%

Benzocaine 5.0%

Purpose

Benzalkonium Chloride .......... First Aid Antiseptic

Benzocaine .......................... Topical Pain Relief

Uses:

First Aid to help prevent infection and for

temporary relief from minor cuts, scrapes and burns

Warnings:

For external use only.

Flammable. Keep away from fire or flame

Do Not Use:

- near eyes or mucous membranes
- on deep or puncture wounds, animal bites or serious burns
- over large areas of the body
- more than one week unless directed by a doctor

Keep Out Of Reach Of Children:

If swallowed, get medical help or contact a Poison Control center right away. 1.800.222.1222

Directions:

- clear affected area
- tear packet open, unfold towelette and apply on area 1 to 3 times daily
- maybe covered with a sterile bandage
- children under 2 ask a doctor

Inactive Ingredients:

isopropyl alcohol. purified water

Product Label

Triple Action

CUT CLEANER
Antiseptic Wipe

1 Premoistened Towelett

- Helps Prevent Infection
- Temporary Relief From Minor Cuts, Scrapes And Burns
- Not For Deep Or Puncture Wounds, Burns Or Animal Bites

NDC# 81238-4616-1

aramark The First Choice In First Aid
Manufactured for aramark Lenexa, KS 66219 913-269-9611

LOT:

res